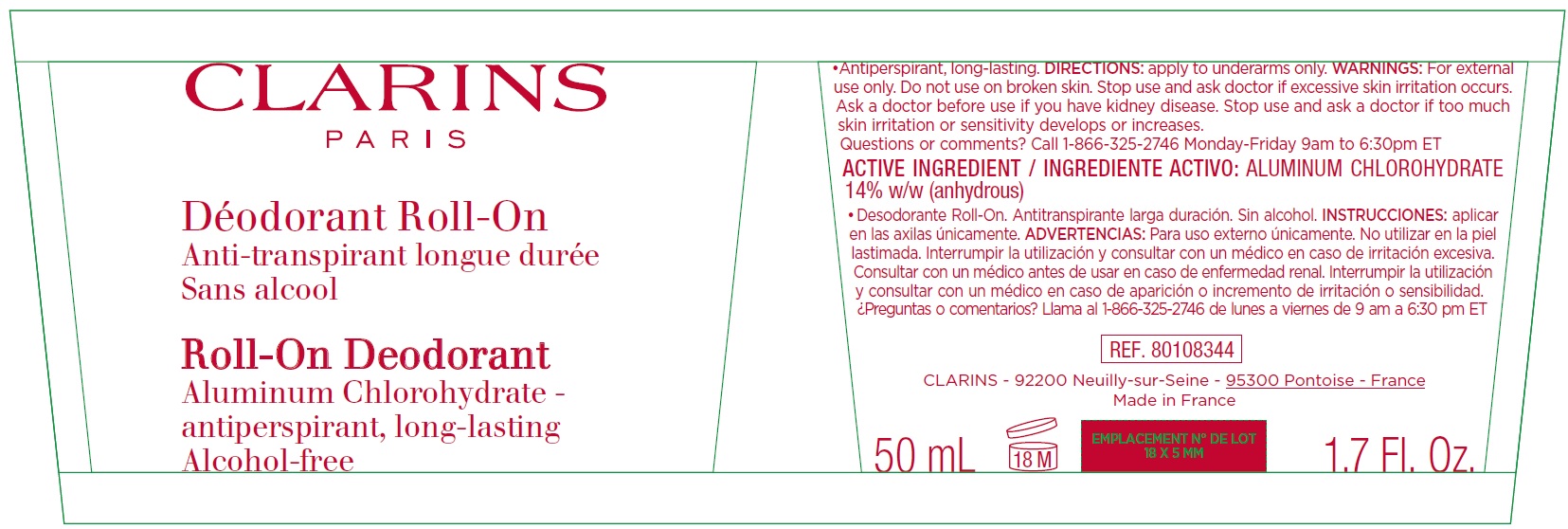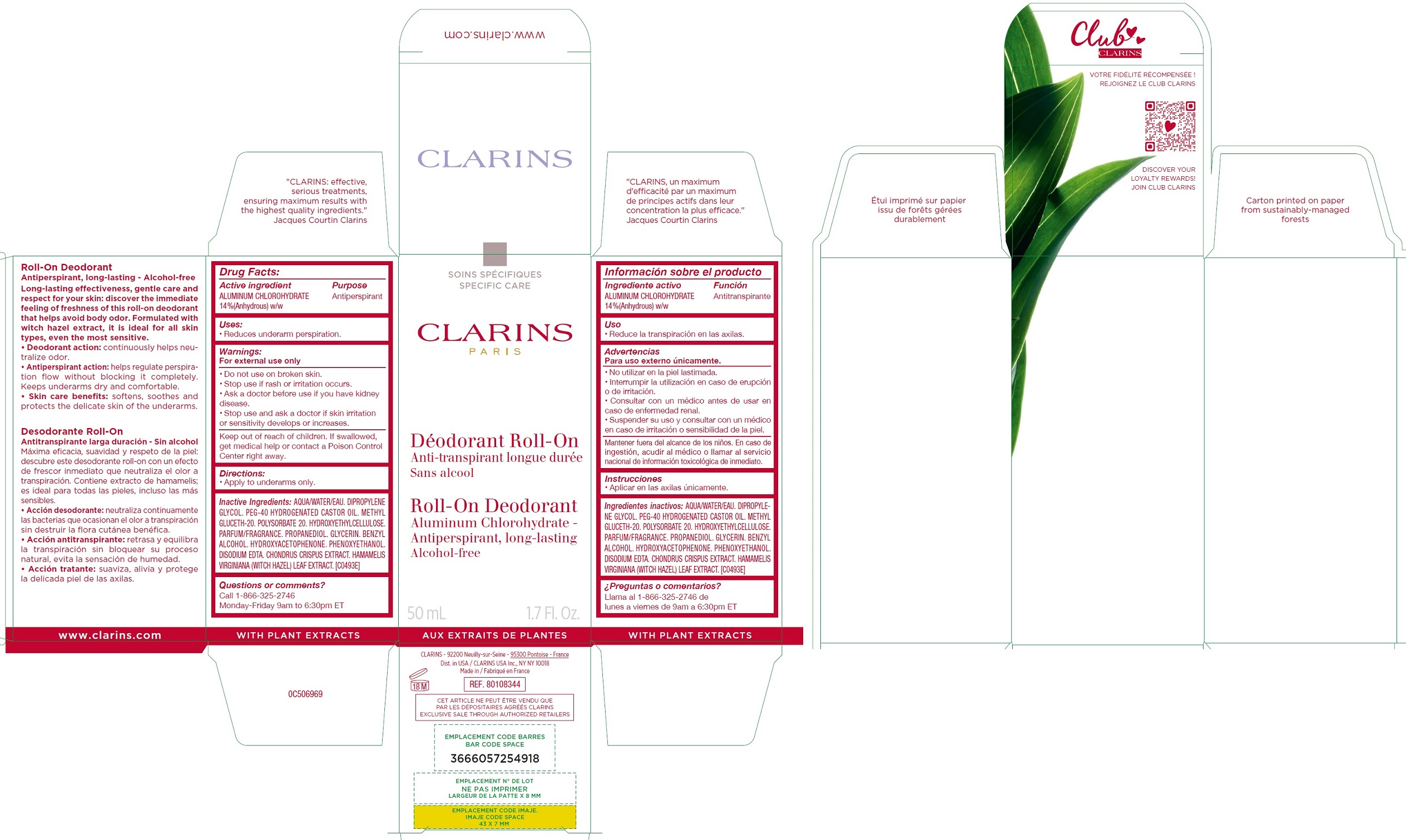 DRUG LABEL: CLARINS - ROLL-ON DEODORANT Aluminum Chlorohydrate - Antiperspirant, Long-lasting Alcohol-free
NDC: 58668-5981 | Form: LIQUID
Manufacturer: Laboratoires Clarins
Category: otc | Type: HUMAN OTC DRUG LABEL
Date: 20240805

ACTIVE INGREDIENTS: ALUMINUM CHLOROHYDRATE 140 mg/1 mL
INACTIVE INGREDIENTS: WATER; DIPROPYLENE GLYCOL; POLYOXYL 40 HYDROGENATED CASTOR OIL; METHYL GLUCETH-20; POLYSORBATE 20; HYDROXYETHYL CELLULOSE, UNSPECIFIED; PROPANEDIOL; GLYCERIN; BENZYL ALCOHOL; HYDROXYACETOPHENONE; PHENOXYETHANOL; EDETATE DISODIUM; CHONDRUS CRISPUS CARRAGEENAN; HAMAMELIS VIRGINIANA LEAF

CLARINS - ROLL-ON DEODORANT Aluminum Chlorohydrate - Antiperspirant, Long-lasting Alcohol-free

Active ingredient

ALUMINUM CHLOROHYDRATE

14 %(Anhydrous) w/w

Purpose

Antiperspirant

Uses:

- Reduces underarm perspiration.

Warnings:

For external use only

Do not use

- on broken skin.
- Stop use if rash or irritation occurs.
- Ask a doctor before use if you have kidney disease.

Stop use and ask a doctor if

skin irritation or sensitivity develops or increases.

Keep out of reach of children.

If swallowed, get medical help or contact a Poison Control Center right away.

Directions:

- Apply to underarms only.

Inactive Ingredients:

AQUA/WATER/EAU. DIPROPYLENE GLYCOL. PEG-40 HYDROGENATED CASTOR OIL. METHYL GLUCETH-20. POLYSORBATE 20. HYDROXYETHYLCELLULOSE. PARFUM/FRAGRANCE. PROPANEDIOL. GLYCERIN. BENZYL ALCOHOL. HYDROXYACETOPHENONE. PHENOXYETHANOL. DISODIUM EDTA. CHONDRUS CRISPUS EXTRACT. HAMAMELIS VIRGINIANA (WITCH HAZEL) LEAF EXTRACT. [C0493E]

Questions or comments?

Call 1-866-325-2746
Monday-Friday 9am to 6:30pm ET